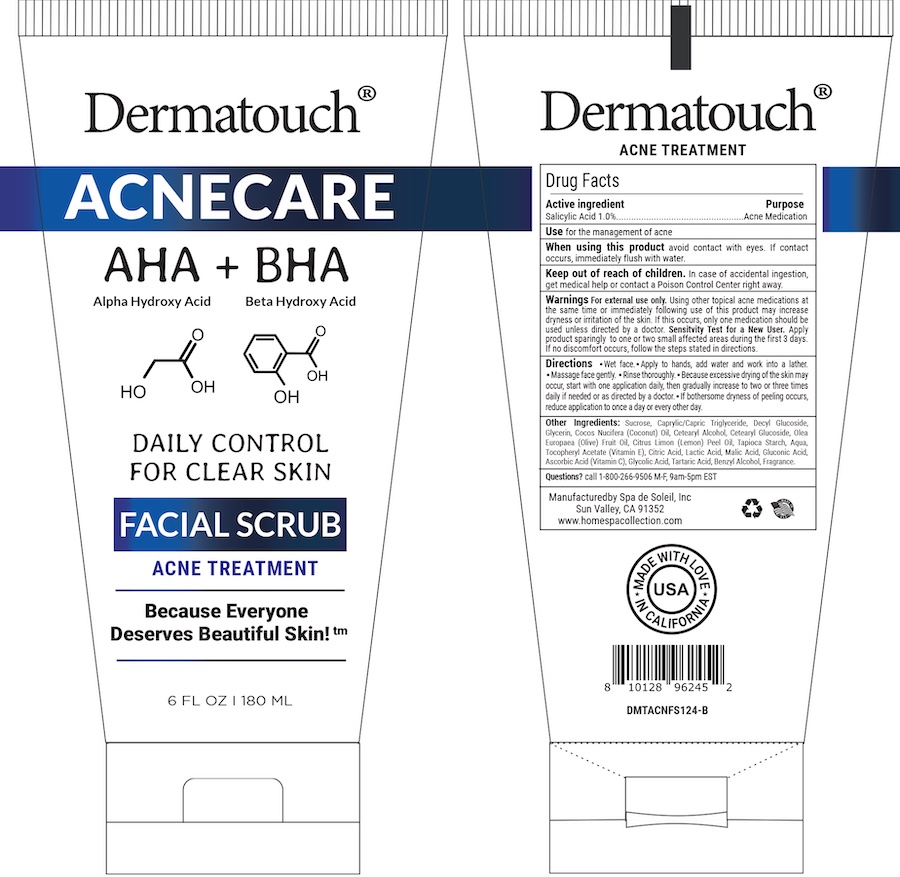 DRUG LABEL: Dermatouch Acnecare Facial Scrub
NDC: 68062-2255 | Form: LIQUID
Manufacturer: Spa de Soleil
Category: otc | Type: HUMAN OTC DRUG LABEL
Date: 20260121

ACTIVE INGREDIENTS: SALICYLIC ACID 1.8 mg/180 mL
INACTIVE INGREDIENTS: CETEARYL GLUCOSIDE; OLIVE OIL; SUCROSE; CAPRYLIC/CAPRIC/LAURIC TRIGLYCERIDE; DECYL GLUCOSIDE; GLYCERIN; COCOS NUCIFERA WHOLE

Dermatouch Acnecare Facial Scrub

Active ingredient Purpose

Salicylic Acid (1.0%)..........Acne Treatment

Purpose

Acne Treatment

INDICATIONS AND USAGE

For treatment of acne

Warnings

For external use only. Using other topical acne medications at the same time or immediately following use of this product may increase dryness or irritation of the skin. If this occurs, only one medication should be used unless directed by a doctor. Sensitivity Test for a New User. Apply product sparingly to one or two small affected areas during the first 3 days. If no discomfort occurs, follow the steps stated in directions.

Keep out of reach of children. In case of accidental ingestion, get medical help or contact a Poison Control Center right away.

When using this product

• Skin irritation and dryness is more likely to occur if you use another topical acne medication while using this product. If irritation occurs, use only one topical acne medication at a time.

Directions:

Wet face. Apply to hands, add water and work into a lather. Massage face gently. Rinse thoroughly. Because excessive drying of the skin may occur, start with one application daily, then gradually increase to two or three times daily if needed or as directed by a doctor..If bothersome dryness of peeling occurs, reduce application to once a day or every other day.

INACTIVE INGREDIENT

Other Ingredients:

Sucrose, Caprylic/Capric Triglyceride, Decyl Glucoside, Glycerin, Cocos Nucifera (Coconut) Oil, Cetearyl Alcohol, Cetearyl Glucoside, Olea Europaea (Olive) Fruit Oil, Citrus Limon (Lemon) Peel Oil, Tapioca Starch, Aqua, Tocopheryl Acetate (Vitamin E), Citric Acid, Lactic Acid, Malic Acid, Gluconic Acid, Ascorbic Acid (Vitamin C), Glycolic Acid, Tartaric Acid, Benzyl Alcohol, Fragrance.